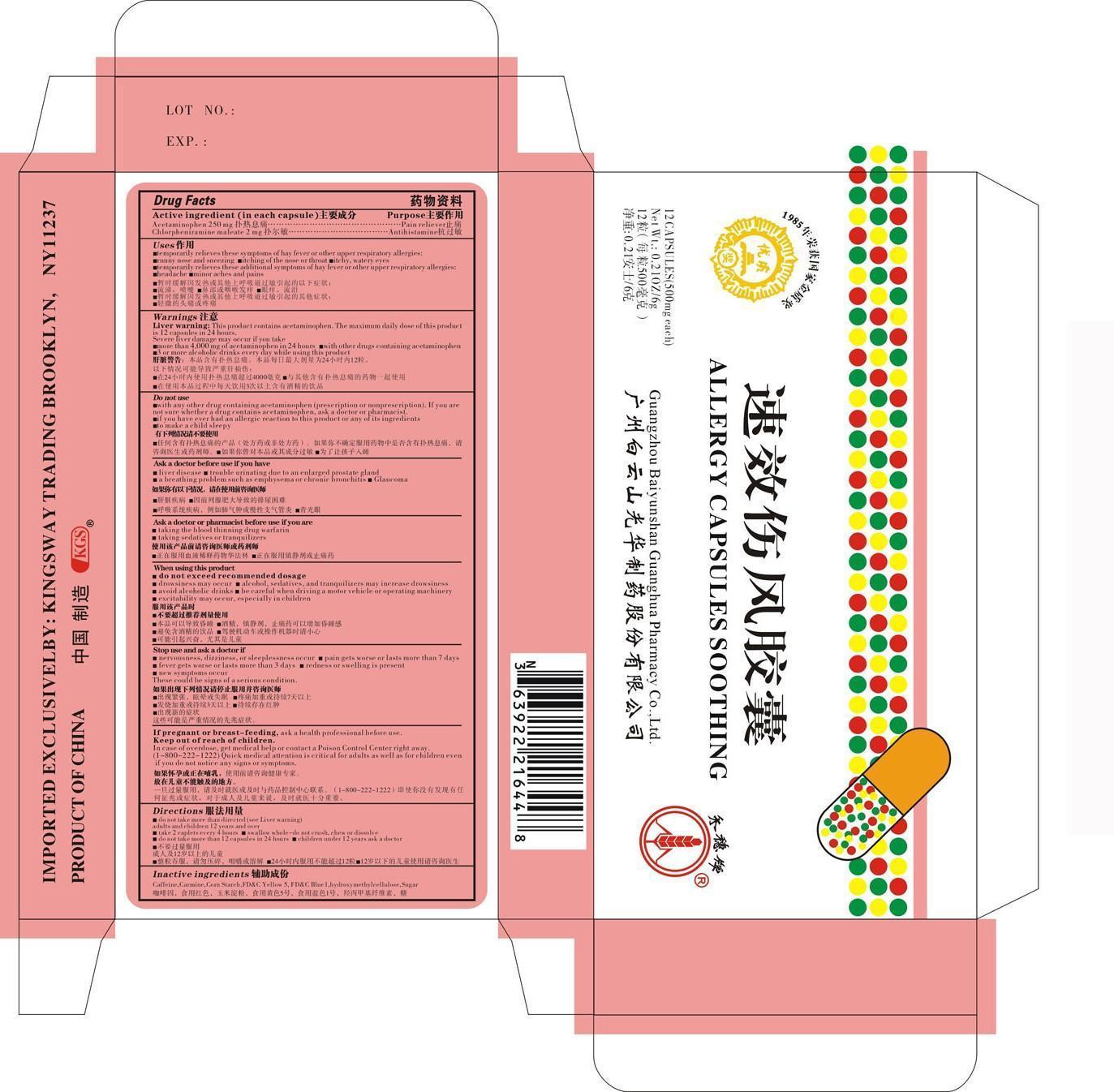 DRUG LABEL: KGS
NDC: 63922-605 | Form: CAPSULE, DELAYED RELEASE PELLETS
Manufacturer: Kingsway
Category: otc | Type: HUMAN OTC DRUG LABEL
Date: 20140226

ACTIVE INGREDIENTS: ACETAMINOPHEN 250 mg/1 1; CHLORPHENIRAMINE MALEATE 2 mg/1 1
INACTIVE INGREDIENTS: CAFFEINE; COCHINEAL; STARCH, CORN; FD&C YELLOW NO. 5; FD&C BLUE NO. 1; HYDROXYMETHYL CELLULOSE; SUCROSE

Drug Facts

Active ingredient (in each capsule)

Acetaminophen 250 mg
Chlorpheniramine Maleate 2 mg

Purpose

Pain reliever

Antihistamine

Uses

■temporarily relieves these symptoms of hay fever and other upper respiratory allergies:

■runny nose and sneezing ■itchy, watery eyes

■temporarily relieves these additional symptoms of hay fever or other respiratory allergies:

■headache ■minor aches and pains

Warnings

Liver warningThis product contains acetaminophen. The maximum daily dose of this product is 12 capsules in 24 hours. Severe liver damage many occur if you take ■ more than 4,000 mg of acetaminophen in 24 hours ■with other drugs containing acetaminophen ■3 or more alcoholic drinks daily while using this product.

Do not use

■with any other drug containing acetaminophen (prescription or nonprescription). If you are not sure whether a drug contains acetaminophen ask a doctor or pharmacist.

■if you have ever had an allergic reactionto this product or any of its ingredients

■to make a child sleepy

Ask a doctor before use if you have

■ liver disease ■ trouble urinating due to an enlarged prostate gland

■ a breathing problem such as emphysema or chronic bronchitis ■ Glaucoma

Ask a doctor or pharmacist if you are

■ taking the blood thinner drug, warfarin

■ taking sedatives or tranquilizers

When using this product

■ do not exceed recommended dosage

■ drowsiness may occur ■alcohol, sedatives and tranquilizers may increase drowsiness

■ avoid alcoholic drinks ■be careful when driving a motor vehicle or operating machinery

■ excitability may occur, especially in children

Stop use and ask a doctor if

■ nervousness, dizziness, or sleepleessness occur ■ pain gets worse or lasts more than 7 days

■ fever gets worse or lasts more than 3 days ■ redness or swelling is present ■ new symptoms occur

This could be signs of a serious condition

If pregnant or breast-feeding

ask a health professional before

Keep out of reach of children

In case of overdose, get medical help or contact a Poison Control Center right away (1-800-222-1222). Quick medical attention is critical for adults as well as for children even if you do not notice any signs of symptoms.

Directions

■ do not take more than directed (see Liver warning)

adults and children 12 years of age and over

■ take 2 caplets every 4 hours. ■swallow whole-do not crush, chew dissolve

■ do not take more than 12 capsules in 24 hours. ■ children under 12 years ask a doctor

Inactive ingredients

Caffeine, Carmine, Corn Starch, FDC Yellow 5, FDC Blue 1,hydroxy methylcellulose, Sugar